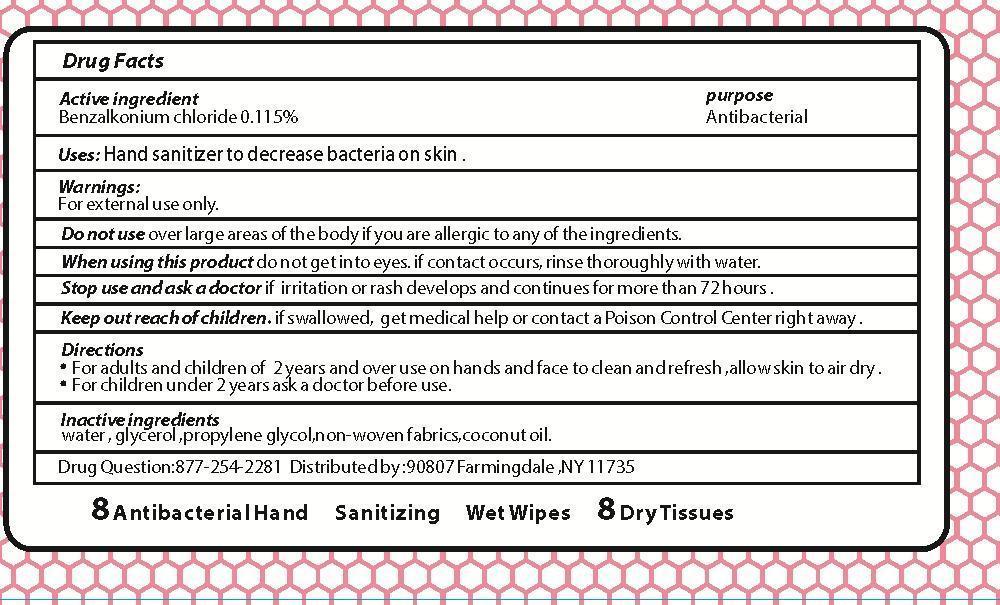 DRUG LABEL: antibacterial Hand Sanitizing wipes
NDC: 69425-001 | Form: swab
Manufacturer: Wuhan Bright Paper Factory
Category: otc | Type: HUMAN OTC DRUG LABEL
Date: 20141203

ACTIVE INGREDIENTS: BENZALKONIUM CHLORIDE 0.115 g/100 g
INACTIVE INGREDIENTS: water; GLYCEROL FORMAL; PROPYLENE GLYCOL; COCONUT OIL

active ingredient

benzalkonium chloride 0.115%

PURPOSE

antibacterial

Use

hand sanitizing to decrease bacteria on the skin

Warnings

For external use only.

Do not use over large areas of the body if you are allergic to any of the ingredients.

When useing this product do not get in eyes. if contact occurs ,rinse throughly with water.

Stop use and ask a doctor if irritation or redness develops and continues for more than 72 hours

Keep out of reach of children

if swallowed,get medical help or contact a Poison Control Center right away.

Directions

For adults and children of 2 years and over use on hands,and face to clean and fresh,allow skin to air dry.

for children under 2 years ask a dcotor before use.

INACTIVE INGREDIENT

water,glycerol,propylene glycol,non-weven fabrics,coconut oil